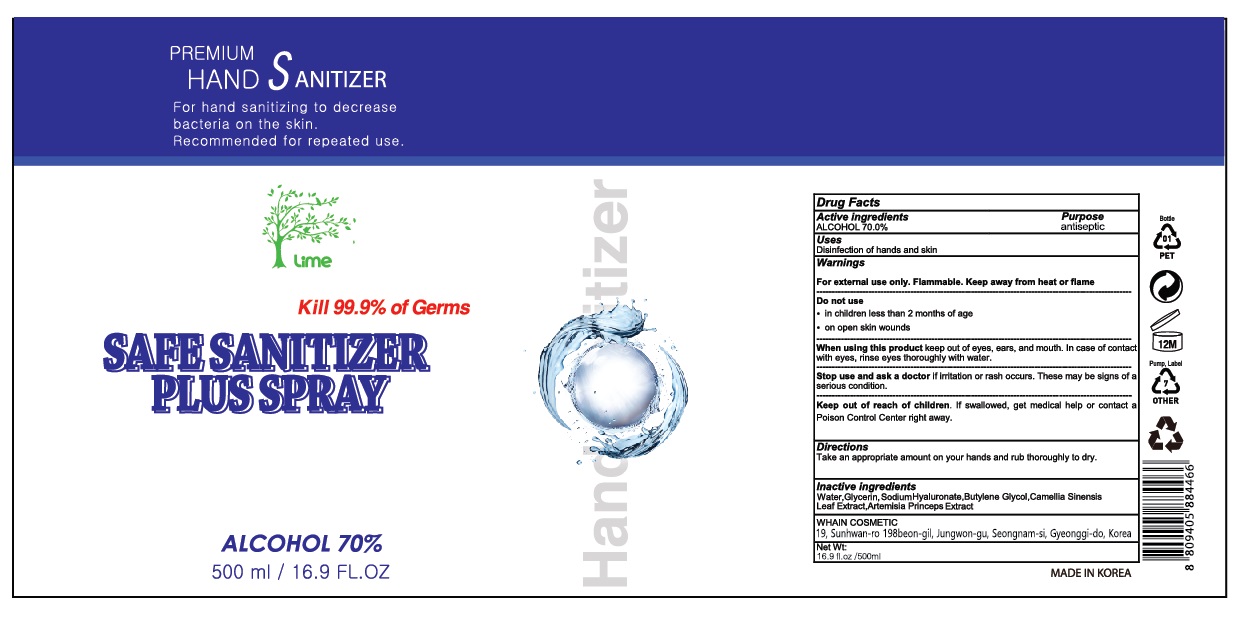 DRUG LABEL: LIME SAFE SANITIZER PLUSspray
NDC: 73823-165 | Form: SPRAY
Manufacturer: WHAIN COSMETIC
Category: otc | Type: HUMAN OTC DRUG LABEL
Date: 20200518

ACTIVE INGREDIENTS: ALCOHOL 350 mL/500 mL
INACTIVE INGREDIENTS: GLYCERIN; HYALURONATE SODIUM; BUTYLENE GLYCOL; WATER; ARTEMISIA PRINCEPS LEAF; GREEN TEA LEAF

[WHAIN COSMETIC] LIME SAFE SANITIZER PLUS SPRAY 500 ml : 73823-165